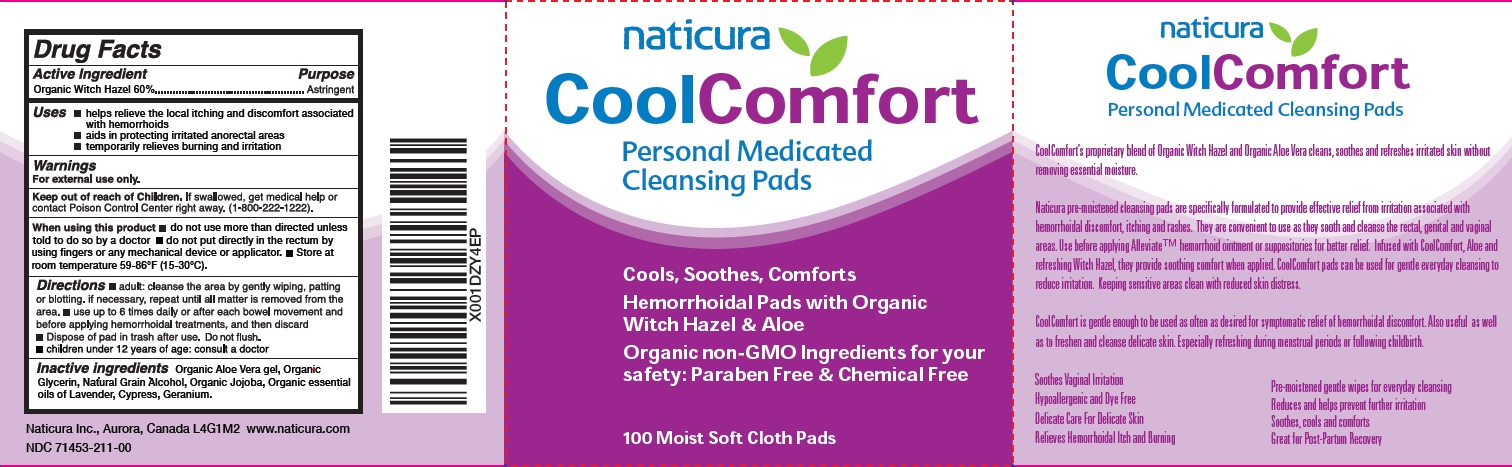 DRUG LABEL: Cool Comfort
NDC: 71453-211 | Form: SWAB
Manufacturer: Naticura Inc
Category: otc | Type: HUMAN OTC DRUG LABEL
Date: 20251205

ACTIVE INGREDIENTS: WITCH HAZEL 60 g/100 g
INACTIVE INGREDIENTS: ALOE VERA LEAF; GLYCERIN; ALCOHOL; JOJOBA OIL

Naticura Cool Comfort

Active Ingredient

Organic Witch hazel 60%

Purpose

Astringent

Uses

- helps relieve the local itching and discomfort associated with hemorrhoids
- aids in protecting irritated anorectal areas.
- temporary relieves burning and irritation.

Warnings

For external use only.

Keep out of reach of children

If swallowed, get medical help or contact a Poison Control Center right away.(1-800-222-1222)

When using this product

- Do not use more than directed unless told to do so by a doctor
- do not put directly into rectum by using fingers or any mechanical device or applicator
- Store at room temperature 59-86oF (15-30^0C)

Directions

- adult: cleanse the area by gently wiping, patting or blotting. If necessary, repeat until all matter is removed from the area.
- use up to 6 times daily or after each bowel movement and before applying hemorrhoidal treatments, and then discard
- Dispose of pad in trash after use.Do not flush
- children under 12 years of age: consult a doctor

Inactive Ingredients

Organic Aloe Vera gel, Organic Glycerin, Natural Grain Alcohol, Organic Jojoba, Organic essential oils of Lavender, Cypress, Geranium.

Principal Display Panel

NDC 71453-211-00

Naticura

CoolComfort

Personal Medicated Cleanisng Pads

Cools, Soothes, Comforts

Hemorrhoidal Pads with Organic Witch Hazel and Aloe

Organic non-GMO Ingredients for your safety: Paraben Free and Chemical Free

100 Moist Soft Cloth Pads